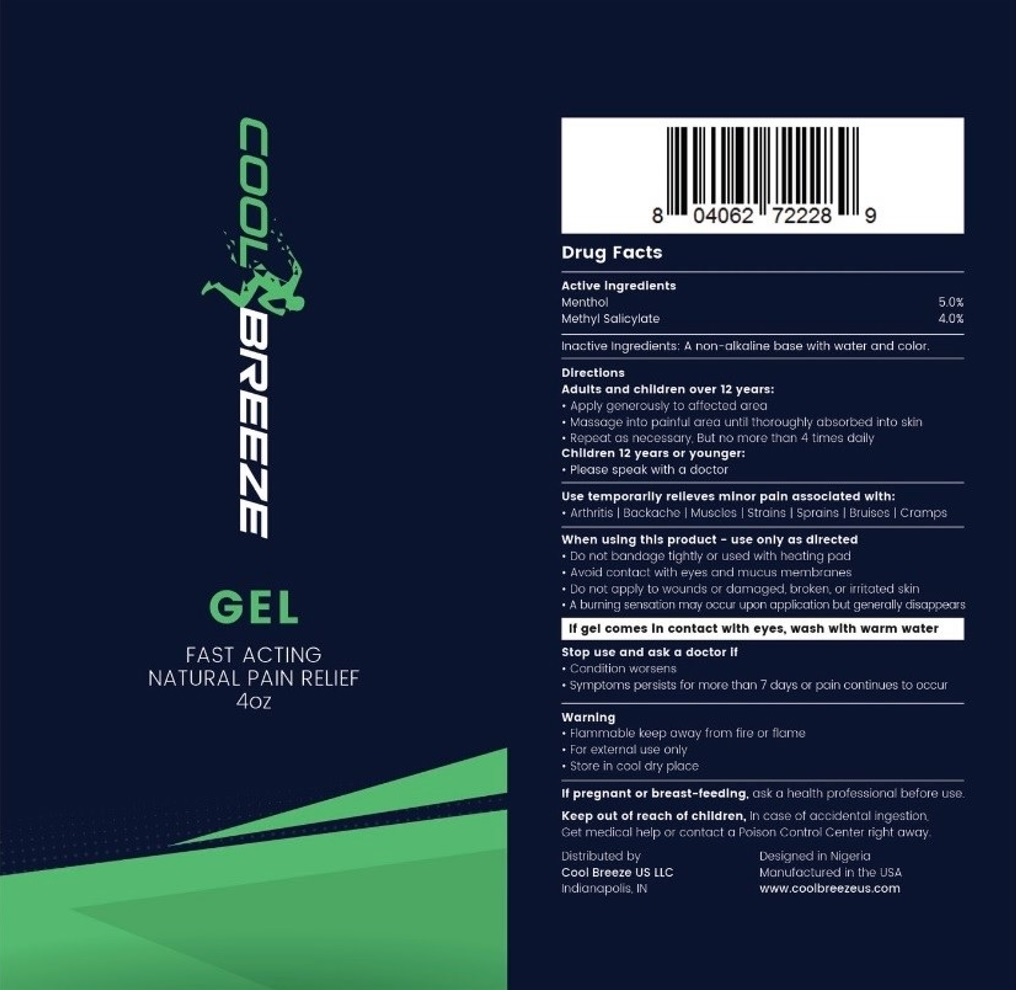 DRUG LABEL: Cool Breeze
NDC: 72744-778 | Form: GEL
Manufacturer: Cool Breeze US LLC
Category: otc | Type: HUMAN OTC DRUG LABEL
Date: 20211203

ACTIVE INGREDIENTS: MENTHOL, UNSPECIFIED FORM 5 g/100 g; METHYL SALICYLATE 4 g/100 g
INACTIVE INGREDIENTS: WATER

COOL BREEZE

Active Ingredients

Menthol 5.0%
Methyl Salicylate 4.0%

Purpose

External analgesic

Use

temporarily relieves minor pain associated with:
• Arthritis | Backache | Muscles | Strains | Sprains | Bruises | Cramps

Warning

• Flammable keep away from fire or flame
• For external use only
• Store in cool dry place

When using this product - use only as directed
• Do not bandage tightly or use with a heating pad
• Avoid contact with eyes and mucus membranes
• Do not apply to wounds or damaged, broken or irritated skin
• A burning sensation may occur upon application but generally disappears

If gel comes in contact with eyes, wash with warm water

Stop use and ask a doctor if
• Condition worsens
• Symptoms persists for more than 7 days or pain continues to occur

If pregnant or breast-feeding, ask a health professional before use.

Keep out of reach of children, In case of accidental ingestion, Get medical help or contact a Poison Control Center right away.

Directions

Adults and children over 12 years:

• Apply generously to affected area.
• Massage into painful area until thoroughly absorbed into skin
• Repeat as necessary, But no more than 4 times daily

Children 12 years or younger:
• Please speak with a doctor

Inactive Ingredients:

A non-alkaline base with water and color.

FAST ACTING NATURAL PAIN RELIEF

Distributed by
Cool Breeze US LLC
Indianapolis, IN

Designed in Nigeria
Manufactured in the USA
www.coolbreezeus.com